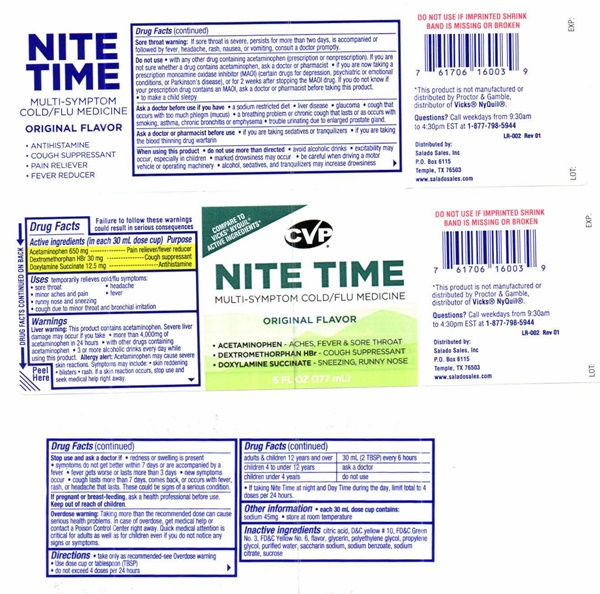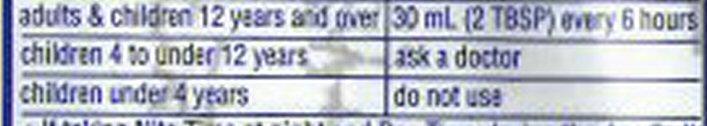 DRUG LABEL: Nite-Time
NDC: 57243-501 | Form: LIQUID
Manufacturer: Salado Sales, Inc.
Category: otc | Type: HUMAN OTC DRUG LABEL
Date: 20231229

ACTIVE INGREDIENTS: ACETAMINOPHEN 650 mg/30 mL; DEXTROMETHORPHAN HYDROBROMIDE 30 mg/30 mL; DOXYLAMINE SUCCINATE 12.5 mg/30 mL
INACTIVE INGREDIENTS: CITRIC ACID MONOHYDRATE; D&C YELLOW NO. 10; FD&C GREEN NO. 3; FD&C YELLOW NO. 6; GLYCERIN; POLYETHYLENE GLYCOL 400; WATER; SACCHARIN SODIUM; SODIUM BENZOATE; SODIUM CITRATE; SUCROSE

Nite Time 501

Drug FactsActive ingredients (in each 30 mL dose cup)

Acetaminophen 650 mg Dextromethorphan HBr 30 mg Doxylamine Succinate 12.5 mg

Purpose

Pain reliever/fever reducer

Cough suppressant

Antihistamine

Keep Out Of Reach Of Children

Uses

temporarily relieves cold/flu symptoms:

- sore throat
- minor aches and pain
- runny nose and sneezing
- cough due to minor sore throat and bronchial irritation
- headache
- fever

Warnings

Failure to follow these warnings could result in serious consequences
Liver warning: This product contains acetaminophen. Severe liver damage may occur if you take

- more than 4 doses in 24 hours, which is the maximum daily amoun
  - with other drugs containing acetaminophen
  - 3 or more alcoholic drinks
- every day while using this product.

Allergy Alert: Acetaminophen may cause severe skin reactions. Symptoms may include

- skin reddening
- blisters
- rash

If a skin reaction ccurs, stop use and seek medical help right away

Sore throat warning: If sore throat is severe, persists for more than 2 days, is accompanied or followed by fever, headache, rash, nausea, or vomiting, consult a doctor promptly.

Ask a doctor before use if you have

- a sodium restricted diet
- liver disease
- glaucoma
- cough that occurs with too much phlegm (mucus)
- a breathing problem or chronic cough that lasts or as occurs with smoking, asthma, chronic bronchitis or emphysema
- trouble urinating due to enlarged prostate gland

Ask A Doctor or Pharmacist before use

- if you are taking sedatives or tranquilizers
- if you are taking the blood thinning drug warfarin

When Using This Product

- do not use more than directed
- avoid alcoholic drinks
- excitability may occur, especially in children
- marked drowsiness may occur
- be careful when driving a motor vehicle or operating machinery
- alcohol, sedatives, and tranquilizers may increase drowsiness

Stop Use And Ask A Doctor If

- redness or swelling is present
- symptoms do not get better within 7 days or are accompanied by a fever
- fever gets worse or lasts more than 3 days
- new symptoms occur
- cough lasts more than 7 days, comes back, or occurs with fever, rash, headache that lasts

Pregnant Or Breast-Feeding

ask a health professional before use.

Overdose Warning

Taking more than the recommended dose can cause serious health problems. In case of overdose, get medical help or contact a Poison Control Center right away. Quick medical attention is critical for adults as well as for children even if you do not notice any signs or symptoms.

Directions

- take only as recommended-see Overdose warnings
- Use dose cup or tablespoon (TBSP)
- do not exceed 4 doses per 24 hours
- If taking Nite Time at night and Day Time during the day, limit total to 4 doses per 24 hours

Other Information

- each 30 mL dose cup contains:
- sodium 45 mg
- store at room temperature

Inactive ingredients

citric acid, D and C yellow No. 10, FD and C Green No. 3, FD and C Yellow No. 6, flavor, glycerin, polyethylene glycol, propylene glycol, purified water, saccharin sodium, sodium benzoate, sodium citrate, sucrose

Do not use

- with any other drug containing acetaminophen (prescription or nonprescription) If you are not sure whether a drug contains acetaminophen, ask a doctor or pharmacist

- if you are now taking a prescription monoamine oxidase inhibitor (MAOI) (certain drugs for depression,psychiatric or emotional conditions, or Parkinson's disease), or for 2 weeks after stopping the MAOI drug. If you do not know if your prescription drug contains an MAOI, ask a doctor or pharmacist before taking this product

- to make a child sleepy

Product Label

Compare to VICKS® NYQUIL® active ingredients CVP CONSUMER VALUE PRODUCTS
Nite-Time COLD/FLU Medicine

Multi-Symptom ORIGINAL FLAVOR
Acetaminophen ..........................Aches, Fever and Sore Throat
Dextromethorphan ......................Cough
Doxylamine Succinate ................Sneezing, Runny nose
6 FL OZ (177 mL)
DO NOT USE IF IMPRINTED SHRINK BAND IS MISSING OR BROKEN
*This product is not manufactured or distributed by Proctor and Gamble, distributor of Vicks® Nyquil® LR-002
Questions? Call weekdays from 9:30am to 4:30pm EST 1-877-795-5944
Distributed by: Salado Sales, Inc. P.O. Box 6115 Temple, TX 76503 www.saladosales.com
LOT: EXP:
Peel Here DRUG FACTS CONTINUED ON BACK
ORIGINAL FLAVOR Nite-Time Multi-Symptom COLD/FLU Medicine

- Antihistamine

- Cough Suppressant

- Pain Reliever

- Fever Reducer

res